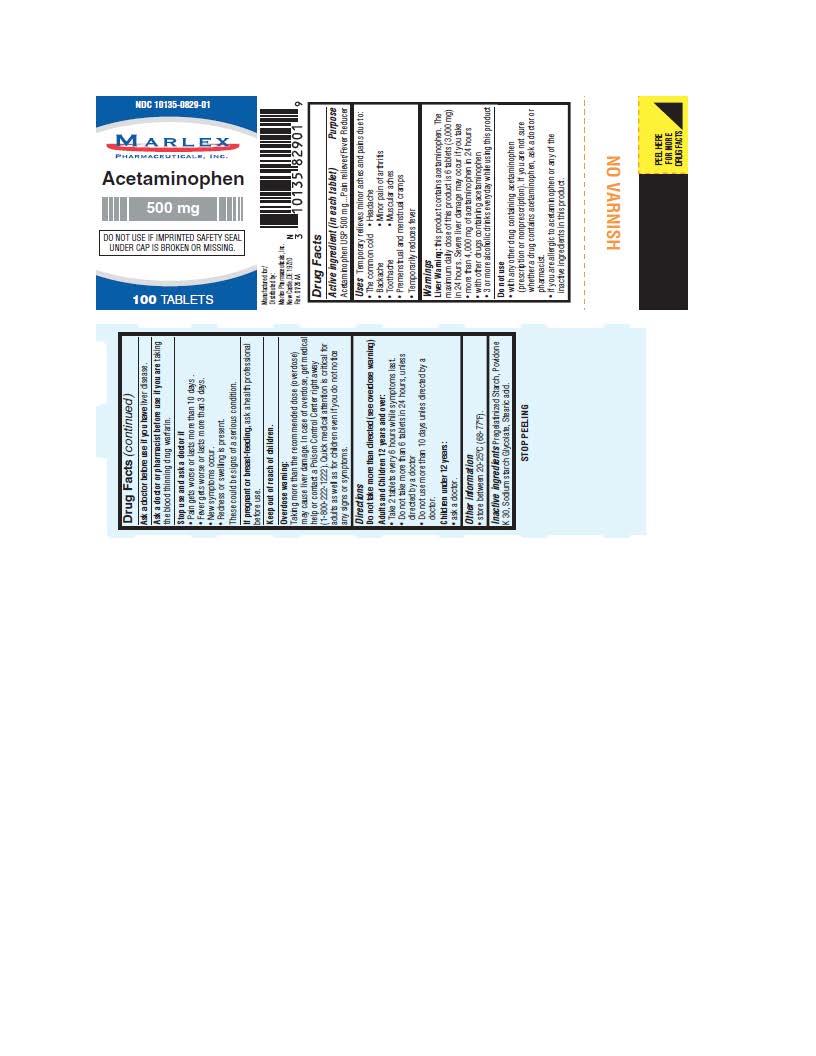 DRUG LABEL: Acetaminophen
NDC: 10135-829 | Form: TABLET
Manufacturer: Marlex Pharmaceuticals Inc
Category: otc | Type: HUMAN OTC DRUG LABEL
Date: 20260201

ACTIVE INGREDIENTS: ACETAMINOPHEN 500 mg/1 1
INACTIVE INGREDIENTS: POVIDONE K30; SODIUM STARCH GLYCOLATE TYPE A POTATO; STARCH, CORN; STEARIC ACID

Acetaminophen 500mg

Drug Facts

Active Ingredient

(in each tablet)

Acetaminophen USP 500 mg

Purpose

Pain Reliever/Fever Reducer

Uses

Temporary relieves minor aches and pains due to:

- The common cold • Headache
- Backache • Minor pain of arthritis
- Toothache • Muscular aches
- Premenstrual and menstrual cramps

* Temporarily reduces fever

Warnings

Liver warning:this product contains acetaminophen. The maximum daily dose of this product is 6 tablets (3,000 mg) in 24 hours. Severe liver damage may occur if you take

- more than 4,000 mg of acetaminophen in 24 hours
- with other drugs containing acetaminophen
- 3 or more alcoholic drinks every day while using this product

Do not use

- with any other drug containing acetaminophen (prescription or nonprescription). If you are not sure whether a drug contains acetaminophen, ask a doctor or pharmacist.
- if you are allergic to acetaminophen or any of the inactive ingredients in this product.

Ask a doctor

before use if you have liver disease.

Ask a doctor or pharmacist

before use if you are taking the blood thinning drug warfarin.

Stop use and ask a doctor if

- Pain gets worse or lasts more than 10 days.
- Fever gets worse or lasts more than 3 days.
- New symptoms occur.
- Redness or swelling is present.

These could be signs of a serious condition.

If pregnant or breast-feeding,

ask a health professional before use.

Overdose warning:

Taking more than the recommended dose (overdose) may cause liver damage. In case of overdose, get medical help or contact a Poison Control Center right away. (1-800-222-1222).

Quick medical attention is critical for adults as well as for children even if you do not notice any signs or symptoms.

Directions

Do not take more than directed (see overdosewarning)

Adults and Children 12 years and over:

- Take 2 tablets every 6 hours while symptoms last.
- Do not take more than 6 tablets in 24 hours, unless directed by a doctor.
- Do not use for more than 10 days unless directed by a doctor.

Children under 12 years:

- ask a doctor.

Other Information

- Store between 20-25 ˚C (68-77 ˚F).

Inactive Ingredients

Pregelatinized Starch, Povidone K 30,Sodium starch Glycolate, Stearic Acid.

Manufactured for/ Distributed by:
Marlex Pharmaceuticals, Inc.
New Castle, DE 19720

Rev. 01/26 AA

Principal Display Panel

NDC 10135-0829-01
ACETAMINOPHEN
500 MG